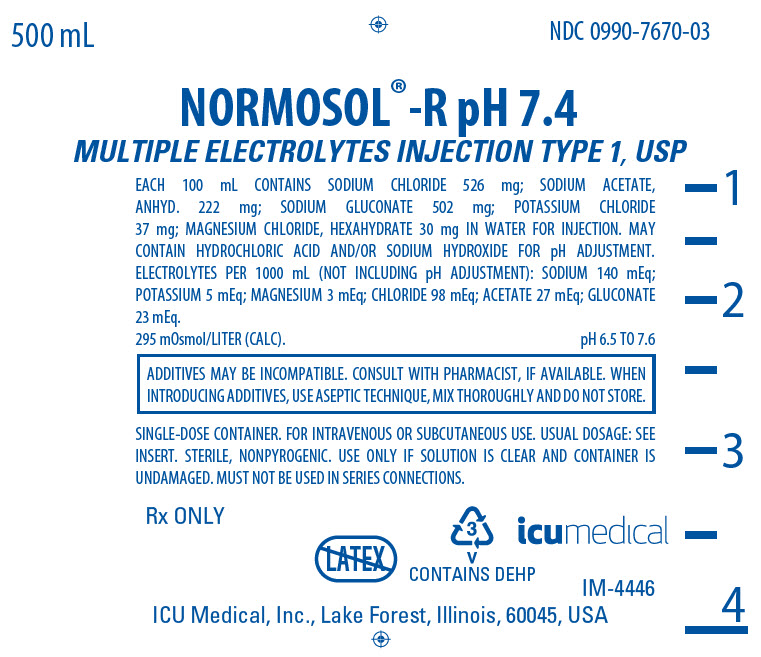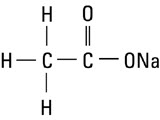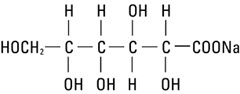 DRUG LABEL: Normosol-R
NDC: 0990-7670 | Form: INJECTION, SOLUTION
Manufacturer: ICU Medical Inc.
Category: prescription | Type: HUMAN PRESCRIPTION DRUG LABEL
Date: 20251030

ACTIVE INGREDIENTS: SODIUM CHLORIDE 526 mg/100 mL; SODIUM ACETATE ANHYDROUS 222 mg/100 mL; SODIUM GLUCONATE 502 mg/100 mL; POTASSIUM CHLORIDE 37 mg/100 mL; MAGNESIUM CHLORIDE 30 mg/100 mL
INACTIVE INGREDIENTS: WATER; HYDROCHLORIC ACID; SODIUM HYDROXIDE

NORMOSOL®-R pH 7.4

MULTIPLE ELECTROLYTES INJECTION TYPE 1, USP

For Replacing Acute Losses of Extracellular Fluid

Flexible Plastic Container

Rx only

DESCRIPTION

Normosol®-R pH 7.4 is a sterile, nonpyrogenic, isotonic solution of balanced electrolytes in water for injection. The solution is administered by intravenous infusion for parenteral replacement of acute losses of extracellular fluid.

Each 100 mL of Normosol-R pH 7.4 contains sodium chloride, 526 mg; sodium acetate, 222 mg; sodium gluconate, 502 mg; potassium chloride, 37 mg; magnesium chloride, hexahydrate 30 mg. May contain hydrochloric acid and/or sodium hydroxide for pH adjustment. pH range 6.5 to 7.6; 295 mOsmol/liter (calc.).

Electrolytes per 1000 mL (not including pH adjustment): Sodium 140 mEq; potassium 5 mEq; magnesium 3 mEq; chloride 98 mEq; acetate 27 mEq; gluconate 23 mEq.

The solution contains no bacteriostat, antimicrobial agent or added buffer (except for pH adjustment) and is intended only for use as a single-dose injection. When smaller doses are required the unused portion should be discarded.

Normosol-R pH 7.4 is a parenteral fluid and electrolyte replenisher.

Sodium Chloride, USP is chemically designated NaCl, a white crystalline powder freely soluble in water.

Potassium Chloride, USP is chemically designated KCl, a white granular powder freely soluble in water.

Magnesium Chloride, USP is chemically designated magnesium chloride, hexahydrate (MgCl2 • 6H2O) deliquescent crystals very soluble in water.

Sodium Acetate, USP is chemically designated sodium acetate, anhydrous (C2H3NaO2), a hygroscopic powder soluble in water. It has the following structural formula:

Sodium gluconate is chemically designated C6H11NaO7, the normal sodium salt of gluconic acid soluble in water. It has the following structural formula:

Water for Injection, USP is chemically designated H2O.

The flexible plastic container is fabricated from a specially formulated polyvinyl chloride. Water can permeate from inside the container into the overwrap but not in amounts sufficient to affect the solution significantly. Solutions in contact with the plastic container may leach out certain chemical components from the plastic in very small amounts; however, biological testing was supportive of the safety of the plastic container materials. Exposure to temperatures above 25°C/77°F during transport and storage will lead to minor losses in moisture content. Higher temperatures lead to greater losses. It is unlikely that these minor losses will lead to clinically significant changes within the expiration period.

CLINICAL PHARMACOLOGY

When administered intravenously, Normosol-R pH 7.4 provides water and electrolytes for replacement of acute extracellular fluid losses without disturbing normal electrolyte relationships. The electrolyte composition approaches that of the principal ions of normal plasma (extracellular fluid). The electrolyte concentration is approximately isotonic in relation to the extracellular fluid (approx. 280 mOsmol/liter) and provides a physiologic sodium to chloride ratio, normal plasma concentrations of potassium and magnesium and two bicarbonate alternates, acetate and gluconate.

Sodium chloride in water dissociates to provide sodium (Na^+) and chloride (Cl^−) ions. Sodium (Na^+) is the principal cation of the extracellular fluid and plays a large part in the therapy of fluid and electrolyte disturbances. Chloride (Cl^−) has an integral role in buffering action when oxygen and carbon dioxide exchange occurs in the red blood cells. The distribution and excretion of sodium (Na^+) and chloride (Cl^−) are largely under the control of the kidney which maintains a balance between intake and output.

Potassium chloride in water dissociates to provide potassium (K^+) and chloride (Cl^−) ions. Potassium is the chief cation of body cells (160 mEq/liter of intracellular water). It is found in low concentration in plasma and extracellular fluids (3.5 to 5.0 mEq/liter in a healthy adult and child over 10 days old; 3.5 to 6.0 mEq/liter in a child less than 10 days old). Potassium plays an important role in electrolyte balance.

Normally about 80 to 90% of the potassium intake is excreted in the urine; the remainder in the stools and to a small extent, in the perspiration. The kidney does not conserve potassium well so that during fasting or in patients on a potassium-free diet, potassium loss from the body continues resulting in potassium depletion.

Magnesium chloride in water dissociates to provide magnesium (Mg^++) and chloride (Cl^−) ions. Magnesium is the second most plentiful cation of the intracellular fluids. It is an important cofactor for enzymatic reactions and plays an important role in neurochemical transmission and muscular excitability. Normal plasma concentration ranges from 1.5 to 2.5 or 3.0 mEq per liter. Magnesium is excreted solely by the kidney at a rate proportional to the plasma concentration and glomerular filtration.

Sodium acetate provides sodium (Na^+) and acetate (CH3COO^−) ions, the latter anion (a source of hydrogen ion acceptors) serving as an alternate source of bicarbonate (HCO3^−) by metabolic conversion in the liver. This has been shown to proceed readily even in the presence of severe liver disease. Thus, acetate anion exerts a mild systemic antiacidotic action that may be advantageous during fluid and electrolyte replacement therapy.

Sodium gluconate provides sodium (Na^+) and gluconate (C6H11O7^−) ions. Although gluconate is a theoretical alternate metabolic source of bicarbonate (HCO3^−) anion, a significant antiacidotic action has not been established. Thus, the gluconate anion serves primarily to complete the cation-anion balance of the solutions.

Water is an essential constituent of all body tissues and accounts for approximately 70% of total body weight. Average normal adult daily requirement ranges from two to three liters (1.0 to 1.5 liters each for insensible water loss by perspiration and urine production).

Average normal pediatric daily requirements are based on the child’s weight as described in the table below:

Weight | Fluid Requirements
Up to 10 kg | 100 mL/kg
11 to 20 kg | 1,000 mL + 50 mL/kg for each kg above 10 kg
Above 20 kg | 1,500 mL + 20 mL/kg for each kg above 20 kg

Water balance is maintained by various regulatory mechanisms. Water distribution depends primarily on the concentration of electrolytes in the body compartments and sodium (Na^+) plays a major role in maintaining physiologic equilibrium.

INDICATIONS AND USAGE

Normosol-R pH 7.4 is indicated for replacement of acute extracellular fluid volume losses in surgery, trauma, burns or shock. Normosol-R pH 7.4 also can be used as an adjunct to restore a decrease in circulatory volume in patients with moderate blood loss. Normosol-R pH 7.4 is not intended to supplant transfusion of whole blood or packed red cells in the presence of uncontrolled hemorrhage or severe reductions of red cell volume.

Normosol-R pH 7.4 is particularly valuable as a solution for use in starting blood, i.e., as a priming solution for the infusion set. No hemolysis of blood is seen at the interface or with mixed solution and blood. It may also be used as a diluent to aid in the transfusion of packed red blood cells (PRBC). Normosol-R pH 7.4 and physiologic saline solution (0.9% Sodium Chloride Injection, USP) are compatible with both young and old PRBC.

CONTRAINDICATIONS

None known.

WARNINGS

Solutions containing sodium ions should be used with great care, if at all, in patients with congestive heart failure, severe renal insufficiency and in clinical states in which there exists edema with sodium retention.

Solutions which contain potassium should be used with great care, if at all, in patients with hyperkalemia, severe renal failure and in conditions in which potassium retention is present.

In patients with diminished renal function, administration of solutions containing sodium or potassium ions may result in sodium or potassium retention. Because elderly patients are more likely to have decreased renal function, care should be taken in dose selection, and it may be useful to monitor renal function during fluid replacement with Normosol-R.

Solutions containing acetate or gluconate ions should be used with great care in patients with metabolic or respiratory alkalosis. Acetate or gluconate should be administered with great care in those conditions in which there is an increased level or an impaired utilization of these ions, such as severe hepatic insufficiency.

The intravenous administration of this solution can cause fluid and/or solute overloading resulting in dilution of serum electrolyte concentrations, overhydration, congested states or pulmonary edema.

Elderly patients may be at increased risk for the development of fluid overloading and dilutional hyponatremia following Normosol-R administration.

The risk of dilutional states is inversely proportional to the electrolyte concentrations of administered parenteral solutions. The risk of solute overload causing congested states with peripheral and pulmonary edema is directly proportional to the electrolyte concentrations of such solutions.

PRECAUTIONS

Normosol-R pH 7.4 should be used with caution in severe renal impairment because of the danger of hyperkalemia. As with all intravenous solutions, care should be taken to avoid circulatory overload, especially in patients with cardiac or pulmonary disorders. Normosol-R pH 7.4 is not intended to correct acidosis or large deficits of individual electrolytes, nor to replace blood or plasma expanders when these are indicated.

Clinical evaluation and periodic laboratory determinations are necessary to monitor changes in fluid balance, electrolyte concentrations and acid-base balance during prolonged parenteral therapy or whenever the condition of the patient warrants such evaluation.

Caution must be exercised in the administration of parenteral fluids, especially those containing sodium ions, to patients receiving corticosteroids or corticotropin.

Solutions containing acetate or gluconate ions should be used with caution, as excess administration may result in metabolic alkalosis.

Do not administer unless solution is clear and container is undamaged. Discard unused portion.

Pregnancy Category C.

Animal reproduction studies have not been conducted with Normosol-R pH 7.4. It is also not known whether this solution can cause fetal harm when administered to a pregnant woman or can affect reproduction capacity. This solution should be given to a pregnant woman only if clearly needed.

Pediatric Use.

The safety and effectiveness of Normosol-R pH 7.4 have been established in the age groups of birth to 16 years. Use of Normosol-R pH 7.4 is supported by evidence from adequate and well-controlled clinical studies in adults with additional data from post-marketing experience in the pediatric population.

Geriatric Use:

Clinical studies of Normosol-R did not include sufficient numbers of subjects aged 65 and over to determine whether they respond differently from younger subjects. Other reported clinical experience has not identified differences in response between elderly and younger patients. In general, dose selection for an elderly patient should be cautious, usually starting at the low end of the dosing range, reflecting the greater frequency of decreased hepatic, renal, or cardiac function, and of concomitant disease or other drug therapy.

Elderly patients have been shown to secrete higher levels of antidiuretic hormone than younger patients, which may increase the risk of fluid overloading, and dilutional hyponatremia in these patients. See WARNINGS.

This drug is known to be substantially excreted by the kidney, and the risk of toxic reactions to this drug may be greater in patients with impaired renal function. Because elderly patients are more likely to have decreased renal function, care should be taken in dose selection, and it may be useful to monitor renal function. See WARNINGS.

Drug Interactions

Additives may be incompatible. Consult with pharmacist, if available. When introducing additives, use aseptic technique, mix thoroughly and do not store.

Normosol-R pH 7.4 does not contain calcium to avoid precipitation of calcium salts that may occur when certain drugs are added. Solutions which contain calcium in amounts exceeding the normal plasma concentration may enhance clotting on contact with citrated blood. Hence, Normosol-R pH 7.4 can be used for starting a blood transfusion.

ADVERSE REACTIONS

Reactions which may occur because of the solution or the technique of administration include febrile response, infection at the site of injection, venous thrombosis or phlebitis extending from the site of injection, extravasation and hypervolemia.

If an adverse reaction does occur, discontinue the infusion, evaluate the patient, institute appropriate therapeutic countermeasures and save the remainder of the fluid for examination if deemed necessary.

OVERDOSAGE

In the event of overhydration or solute overload, re-evaluate the patient and institute appropriate corrective measures. See WARNINGS, PRECAUTIONS and ADVERSE REACTIONS.

DOSAGE AND ADMINISTRATION

Normosol-R pH 7.4 is administered by intravenous infusion. It may also be administered subcutaneously. The amount to be infused is based on replacement of losses of extracellular fluid volume in the individual patient. Up to three times the volume of estimated blood loss during and after surgery can be given to correct circulatory volume when there is only a moderate loss of blood.

Parenteral drug products should be inspected visually for particulate matter or discoloration prior to administration, whenever solution and container permit. See PRECAUTIONS.

INSTRUCTIONS FOR USE

To Open

Tear outer wrap at notch and remove solution container. Some opacity of the plastic due to moisture absorption during the sterilization process may be observed. This is normal and does not affect the solution quality or safety. The opacity will diminish gradually. If supplemental medication is desired, follow directions below before preparing for administration.

To Add Medication

1. Prepare additive port.
2. Using aseptic technique and an additive delivery needle of appropriate length, puncture resealable additive port at target area, inner diaphragm and inject. Withdraw needle after injecting medication.
3. The additive port may be protected by covering with an additive cap.
4. Mix container contents thoroughly.

To Administer

1. Attach administration set per manufacturer’s instructions.
2. Regulate rate of administration per institutional policy.

WARNING: DO NOT USE FLEXIBLE CONTAINER IN SERIES CONNECTIONS.

HOW SUPPLIED

Normosol-R pH 7.4 (Multiple Electrolytes Injection Type 1, USP) is supplied in 500 and 1000 mL single-dose flexible plastic containers

NDC 0409-7670-03 [Manufactured for ICU Medical, Inc., Lake Forest, Illinois, 60045, USA]

NDC 0990-7670-03,

NDC 0409-7670-09 [Manufactured by ICU Medical, Inc., Lake Forest, Illinois, 60045, USA] ,

NDC 0990-7670-09,

ICU Medical is transitioning NDC from the "0409" to a "0990" labeler code. Both NDC codes are expected to be in the market for a period of time.

Exposure of pharmaceutical products to heat should be minimized. Store at 20 to 25°C (68 to 77°F). [See USP Controlled Room Temperature.]

Revised: August, 2020

IFU0000259

PRINCIPAL DISPLAY PANEL - 500 mL Bag Label

500 mL
NDC 0990-7670-03

NORMOSOL®-R pH 7.4
MULTIPLE ELECTROLYTES INJECTION TYPE 1, USP

EACH 100 mL CONTAINS SODIUM CHLORIDE 526 mg; SODIUM ACETATE,
ANHYD. 222 mg; SODIUM GLUCONATE 502 mg; POTASSIUM CHLORIDE
37 mg; MAGNESIUM CHLORIDE, HEXAHYDRATE 30 mg IN WATER FOR INJECTION. MAY
CONTAIN HYDROCHLORIC ACID AND/OR SODIUM HYDROXIDE FOR pH ADJUSTMENT.
ELECTROLYTES PER 1000 mL (NOT INCLUDING pH ADJUSTMENT): SODIUM 140 mEq;
POTASSIUM 5 mEq; MAGNESIUM 3 mEq; CHLORIDE 98 mEq; ACETATE 27 mEq; GLUCONATE
23 mEq.
295 mOsmol/LITER (CALC).
pH 6.5 TO 7.6

ADDITIVES MAY BE INCOMPATIBLE. CONSULT WITH PHARMACIST, IF AVAILABLE. WHEN
INTRODUCING ADDITIVES, USE ASEPTIC TECHNIQUE, MIX THOROUGHLY AND DO NOT STORE.

SINGLE-DOSE CONTAINER. FOR INTRAVENOUS OR SUBCUTANEOUS USE.USUAL DOSAGE: SEE
INSERT. STERILE, NONPYROGENIC. USE ONLY IF SOLUTION IS CLEAR AND CONTAINER IS
UNDAMAGED. MUST NOT BE USED
IN SERIES CONNECTIONS.

Rx ONLY

3
v
CONTAINS DEHP

icumedical

IM-4446

ICU Medical, Inc., Lake Forest, Illinois, 60045, USA